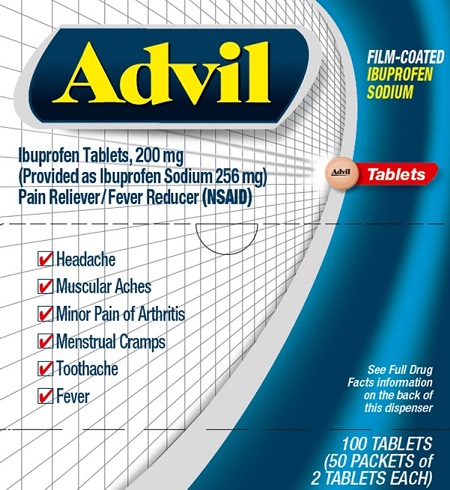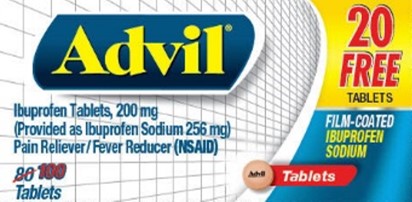 DRUG LABEL: Advil
NDC: 0573-0133 | Form: TABLET, COATED
Manufacturer: Haleon US Holdings LLC
Category: otc | Type: HUMAN OTC DRUG LABEL
Date: 20251003

ACTIVE INGREDIENTS: IBUPROFEN SODIUM 256 mg/1 1
INACTIVE INGREDIENTS: ACESULFAME POTASSIUM; CARAMEL; CARNAUBA WAX; SILICON DIOXIDE; COPOVIDONE K25-31; FERRIC OXIDE RED; HYPROMELLOSE, UNSPECIFIED; MANNITOL; MEDIUM-CHAIN TRIGLYCERIDES; MICROCRYSTALLINE CELLULOSE; POLYETHYLENE GLYCOL, UNSPECIFIED; PROPYLENE GLYCOL; SODIUM LAURYL SULFATE; SUCRALOSE; TITANIUM DIOXIDE

Advil IBU Sodium NDC 0573-0133, 0573-0134

Active ingredient (in each tablet)

Ibuprofen 200 mg (provided as ibuprofen sodium 256 mg) (NSAID)*

*nonsteroidal anti-inflammatory drug

Purpose

Pain reliever/ Fever reducer

Uses

- temporarily relieves minor aches and pains due to:
  - headache
  - toothache
  - backache
  - menstrual cramps
  - the common cold
  - muscular aches
  - minor pain of arthritis
- temporarily reduces fever

Warnings

Allergy alert:

Ibuprofen may cause a severe allergic reaction, especially in people allergic to aspirin. Symptoms may include:

- hives
- facial swelling
- asthma (wheezing)
- shock
- skin reddening
- rash
- blisters

If an allergic reaction occurs, stop use and seek medical help right away.

Stomach bleeding warning:

This product contains an NSAID, which may cause severe stomach bleeding. The chance is higher if you:

- are age 60 or older
- have had stomach ulcers or bleeding problems
- take a blood thinning (anticoagulant) or steroid drug
- take other drugs containing prescription or nonprescription NSAIDs [aspirin, ibuprofen, naproxen, or others]
- have 3 or more alcoholic drinks every day while using this product
- take more or for a longer time than directed

Heart attack and stroke warning

NSAIDs, except aspirin, increase the risk of heart attack, heart failure, and stroke. These can be fatal. The risk is higher if you use more than directed or for longer than directed.

Do not use

- if you have ever had an allergic reaction to any other pain reliever/fever reducer
- right before or after heart surgery

Ask a doctor before use if

- stomach bleeding warning applies to you
- you have problems or serious side effects from taking pain relievers or fever reducers
- you have a history of stomach problems, such as heartburn
- you have high blood pressure, heart disease, liver cirrhosis, kidney disease, asthma, or had a stroke
- you are taking a diuretic

Ask a doctor or pharmacist before use if you are

- under a doctor's care for any serious condition
- taking aspirin for heart attack or stroke, because ibuprofen may decrease this benefit of aspirin
- taking any other drug

When using this product

- take with food or milk if stomach upset occurs

Stop use and ask a doctor if

- you experience any of the following signs of stomach bleeding:
  - feel faint
  - vomit blood
  - have bloody or black stools
  - have stomach pain that does not get better
- you have symptoms of heart problems or stroke:
  - chest pain
  - trouble breathing
  - weakness in one part or side of body
  - slurred speech
  - leg swelling
- pain gets worse or lasts more than 10 days
- fever gets worse or lasts more than 3 days
- redness or swelling is present in the painful area
- any new symptoms appear

PREGNANCY OR BREAST FEEDING

If pregnant or breast-feeding,ask a health professional before use. It is especially important not to use ibuprofen at 20 weeks or later in pregnancy unless definitely directed to do so by a doctor because it may cause problems in the unborn child or complications during delivery.

Keep out of reach of children.In case of overdose, get medical help or contact a Poison Control Center right away.

Directions

- do not take more than directed
- the smallest effective dose should be used
- adults and children 12 years and over: take 1 tablet every 4 to 6 hours while symptoms persist
- if pain or fever does not respond to 1 tablet, 2 tablets may be used
- do not exceed 6 tablets in 24 hours, unless directed by a doctor
- children under 12 years: ask a doctor

Other information

- each tablet contains: sodium 22 mg
- read all warnings and directions before use.
- store at 20-25°C (68-77°F)
- avoid excessive heat above 40°C (104°F)

Inactive ingredients

acesulfame potassium, caramel color, carnauba wax, colloidal silicon dioxide, copovidone, ferric oxide, hypromellose, mannitol, medium-chain triglycerides, microcrystalline cellulose, natural and artificial flavor, pharmaceutical ink, polyethylene glycol, propylene glycol, sodium lauryl sulfate, sucralose, titanium dioxide

Questions or comments?

Call weekdays 9 AM to 5 PM EST at 1-800-88-ADVIL

Additional Information

Do Not Use if the sealed child resistant pouch is broken or torn.

For most recent product information, visit www.Advil.com

PRINCIPAL DISPLAY PANEL

Advil

FILM-COATED
IBUPROFEN
SODIUM

Ibuprofen Tablets, 200 mg
(Provided as Ibuprofen Sodium 256 mg)
Pain Reliever / Fever Reducer (NSAID)

Advil Tablets

- Headache
- Muscular Aches
- Minor Pain of Arthritis
- Menstrual Cramps
- Toothache
- Fever

See Full Drug Facts information on the back of this dispenser

100 TABLETS

(50 PACKETS of 2 TABLETS EACH)

000068427 Front Carton

PRINCIPAL DISPLAY PANEL

Advil®

20
FREE
TABLETS

Ibuprofen Tablets, 200 mg
(Provided as Ibuprofen Sodium 256 mg)
Pain Reliever / Fever Reducer (NSAID)

FILM-COATED
IBUPROFEN
SODIUM

Advil Tablets

100
Tablets